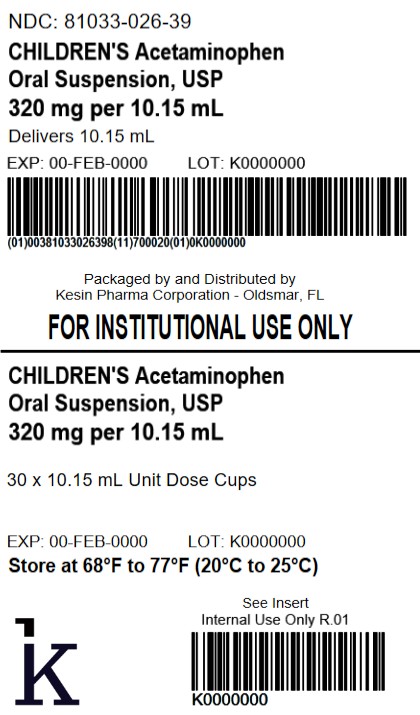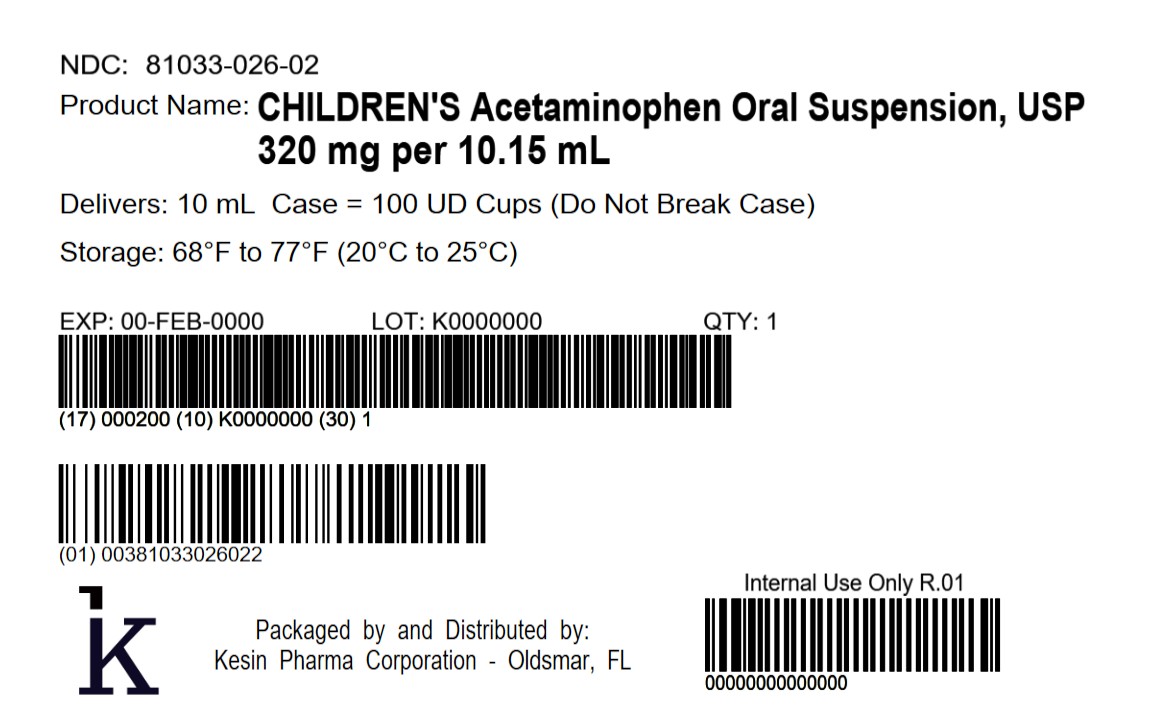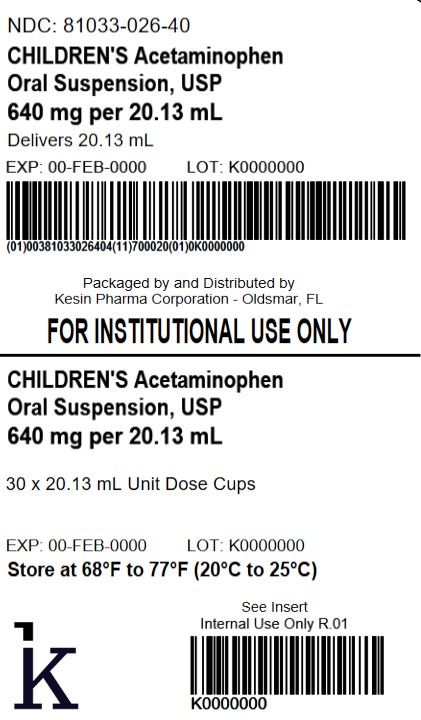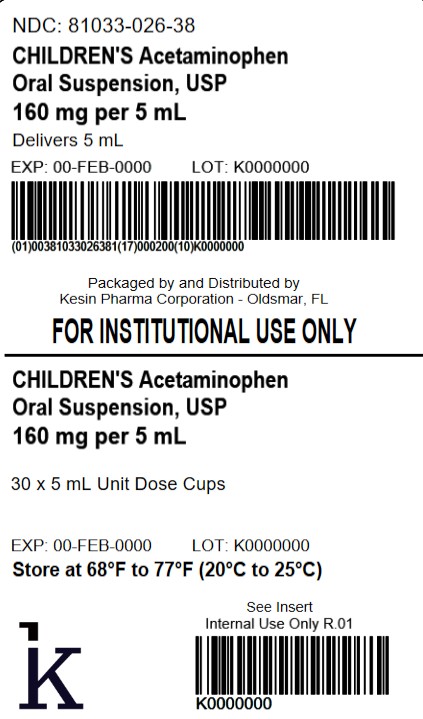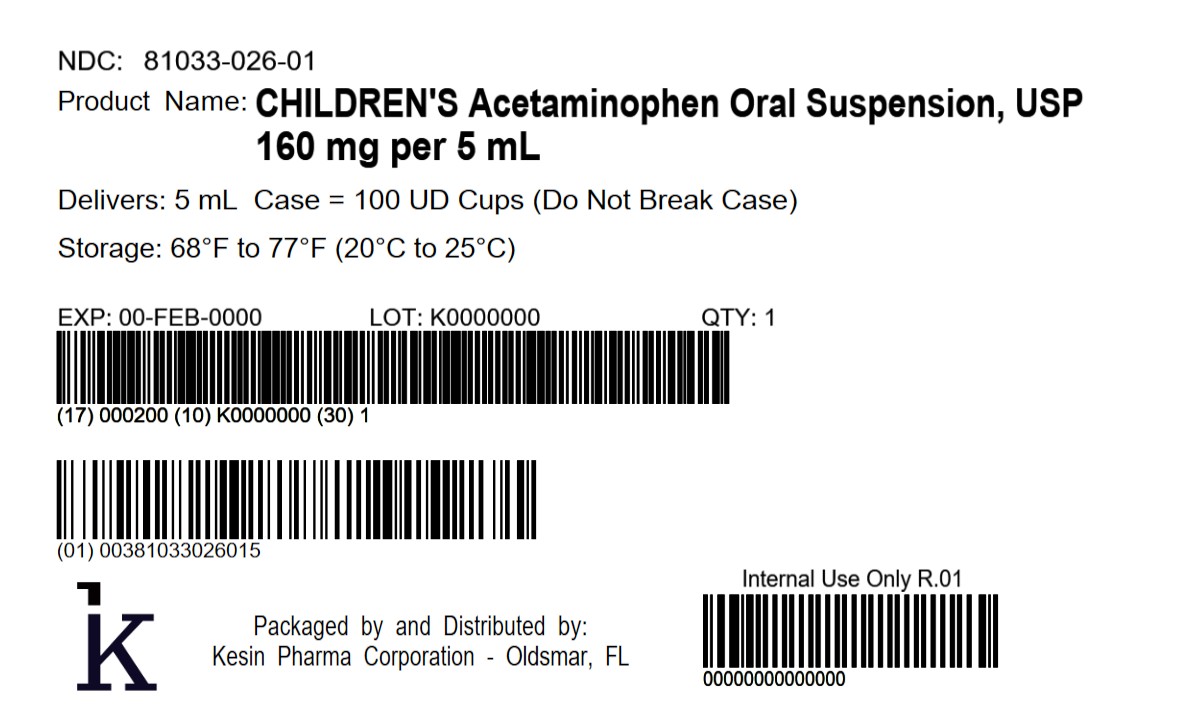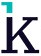 DRUG LABEL: CHILDRENS Acetaminophen
NDC: 81033-026 | Form: SUSPENSION
Manufacturer: Kesin Pharma Corporation
Category: otc | Type: HUMAN OTC DRUG LABEL
Date: 20260216

ACTIVE INGREDIENTS: ACETAMINOPHEN 160 mg/5 mL
INACTIVE INGREDIENTS: CARBOXYMETHYLCELLULOSE; WATER; CITRIC ACID; SORBITOL; SUCRALOSE; GLYCERIN; CELLULOSE, MICROCRYSTALLINE; POTASSIUM SORBATE; SUCROSE; XANTHAN GUM

CHILDREN'S Acetaminophen Oral Suspension, USP

Active ingredient (in each 5 mL)

Acetaminophen 160 mg

PURPOSE

Pain Reliever/Fever Reducer

USES

Temporarily reduces fever
Temporarily relieves minor aches and pains due to:

- the common cold
- flu
- headaches
- sore throat
- toothaches

WARNINGS

Liver warning: This product contains acetaminophen. Severe liver damage may occur if your child takes:

- more than 5 doses in 24 hours, which is the maximum daily amount
- with other drugs containing acetaminophen

Allergy alert: Acetaminophen may cause severe skin reactions.

Symptoms may include:

- skin reddening
- blisters
- rash

If a skin reaction occurs, stop use and seek medical help right away
Sore throat warning: If sore throat is severe, persistent for more than 2 days, is accompanied
or followed by fever, headache, nausea, rash, or vomiting, consult a doctor promptly.

Do not use

- with any other drug containing acetaminophen (prescription or nonprescription). If you are not sure whether a drug contains acetaminophen, ask a doctor or pharmacist.
- if your child is allergic to acetaminophen or any of the inactive ingredients in this product

Ask a doctor before use if the your child has liver disease
Ask a doctor or pharmacist before use if your child is taking the blood thinning drug warfarin.
When using this product, do not exceed the recommended dose (see overdose warning)

Stop use and ask a doctor if

- symptoms do not improve
- new symptoms occur
- pain gets worse or lasts more than 5 days
- fever gets worse or lasts more than 3 days
- redness or swelling is present

These could be signs of a serious condition.

Keep out of reach of children.

OVERDOSAGE

Overdose warning: In case of overdose, get medical help or contact a Poison Control Center right away. Quick medical attention is critical for adults as well as for children even if you do not notice any signs or symptoms.

DIRECTIONS

- this product does not contain directions or complete warnings for adult use
- do not take more than directed (see overdose warning)
- shake well before using
- mL = milliliter
- find the right dose on chart below. If possible, use weight to dose; otherwise, use age
- repeat dose every 4 hours while symptoms last
- do not give more than 5 times in 24 hours

Weight (lb) | Age (yr) | Dose (mL)
Under 24 | Under 2 years | Ask a doctor
24 to 35 | 2 to 3 years | 5 mL
36 to 47 | 4 to 5 years | 7.5 mL
48 to 59 | 6 to 8 years | 10 mL
60 to 71 | 9 to 10 years | 12.5 mL
72 to 95 | 11 years | 15 mL

* or as directed by a doctor

Other information

- each 5 mL contains: sodium: < 5 mg
- store at 20°C to 25°C (68°F to 77°F) [See USP Controlled Room Temperature]
- protect from freezing
- a white to off-white, cherry flavored suspension supplied in the following oral dosage forms

NDC 81033-026-05: 5 mL unit-dose cup
NDC 81033-026-38: Carton containing 30 unit-dose cups of 5 mL each.
NDC 81033-026-01: Case containing 100 unit-dose cups of 5 mL each.
NDC 81033-026-10: 10.15 mL unit-dose cup
NDC 81033-026-39: Carton containing 30 unit-dose cups of 10.15 mL each.
NDC 81033-026-02: Case containing 100 unit-dose cups of 10.15 mL each.
NDC 81033-026-20: 20.13 mL unit-dose cup
NDC 81033-026-40: Carton containing 30 unit-dose cups of 20.13 mL each.

Inactive ingredients

carboxymethylcellulose sodium, cherry flavor, citric acid, glycerin, microcrystalline cellulose, potassium sorbate, purified water, sorbitol, sucralose, sucrose, and xanthan gum.

Questions or comments?

Call 1-833-537-4679

Distributed by:
Kesin Pharma
Oldsmar, FL 34677
PIS-026-V01
Rev. 02/2026

PACKAGE LABEL

NDC 81033-026-38

CHILDREN'S Acetaminophen Oral Suspension, USP

160 mg per 5 mL

30 x 5 mL Unit Dose Cups

PACKAGE LABEL

NDC 81033-026-01

CHILDREN'S Acetaminophen Oral Suspension, USP

160 mg per 5 mL

100 UD Cups (Do Not Break Case)

PACKAGE LABEL

NDC 81033-026-39

CHILDREN'S Acetaminophen Oral Suspension, USP

320 mg per 10.15 mL

30 x 10.15 mL Unit Dose Cups

PACKAGE LABEL

NDC 81033-026-02

CHILDREN'S Acetaminophen Oral Suspension, USP

320 mg per 10.15 mL

100 UD Cups (Do Not Break Case)

PACKAGE LABEL

NDC 81033-026-40

CHILDREN'S Acetaminophen Oral Suspension, USP

640 mg per 20.13 mL

30 x 20.13 mL Unit Dose Cups